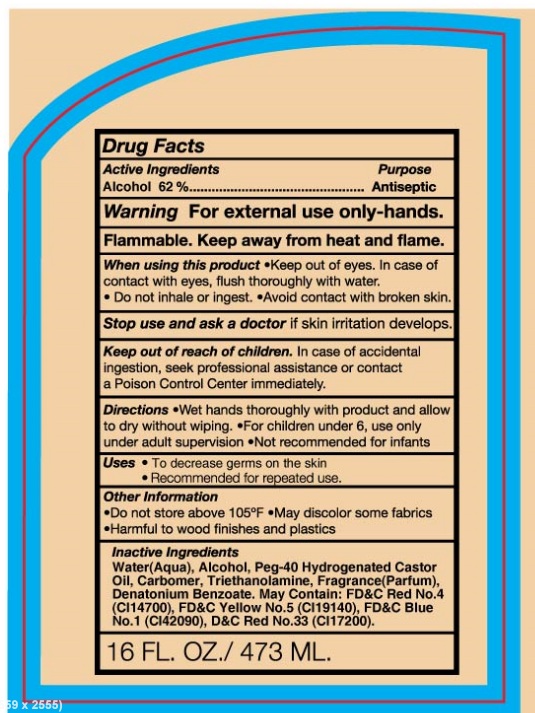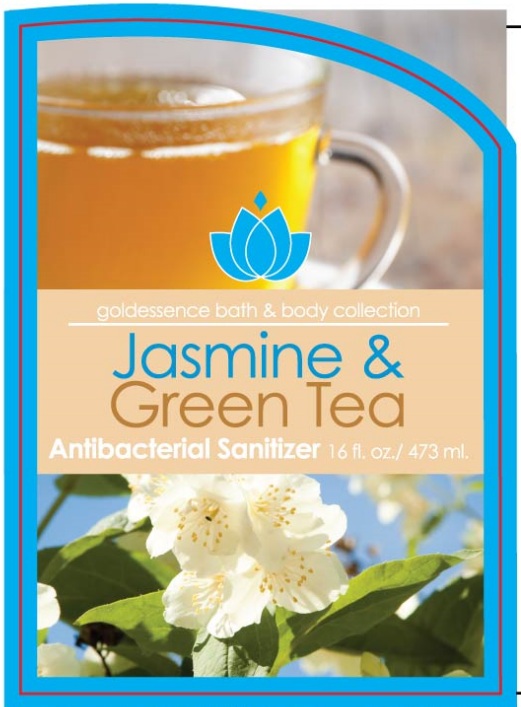 DRUG LABEL: JASMINE AND GREEN TEA ANTIBACTERIAL SANITIZER
NDC: 51201-202 | Form: LIQUID
Manufacturer: Goldessence, Limited
Category: otc | Type: HUMAN OTC DRUG LABEL
Date: 20100725

ACTIVE INGREDIENTS: ALCOHOL 62 mL/100 mL
INACTIVE INGREDIENTS: WATER; TROLAMINE; DENATONIUM BENZOATE

JASMINE AND GREEN TEA ANTIBACTERIAL SANITIZER

Drug Facts

Active Ingredients.........................purpose

Alcohol 62%.....................................antiseptic

WARNINGS

Warning. For external use only-hands

Flammable keep away from heat and flame

When using this product. keep out of eyes. In case of contact with eyes, flush thoroughly with water,

do not inhale or ingest. avoid contact with broken skin.

Stop use and ask a doctor if skin irritation develops.

keep out of reach of children. In case of accidental ingestion, seek professional assistance or contact a poison control center immediately.

Directions

Wet hands thoroughly with product and allow to dry with out wiping

For children under 6, use only under adult supervision

not recommended for infants.

Uses:

To decrease germs on the skin

recommended for repeated use.

Other Information

Do not store above 105oC

May discolor some fabrics

Harmful to wood finishes and plastics

Inactive Ingredients

Water (aqua), Alcohol, Peg-40 Hydrogenated Castor Oil, Carbomer, Triethanolamine, Fragrance (parfum) Denatonium Benzoate. May contain FD and C Red No4 (CI14700), FD and C yellow No 5 (CI 19140), FD and C blue no1(CI42090), Dand C Red No 33 (CI17200)

16fl oz/473 ml

PACKAGE LABEL

goldessence bath and body collection

Jasmine and Green Tea
Antibacterial Sanitizer 16floz / 473ml